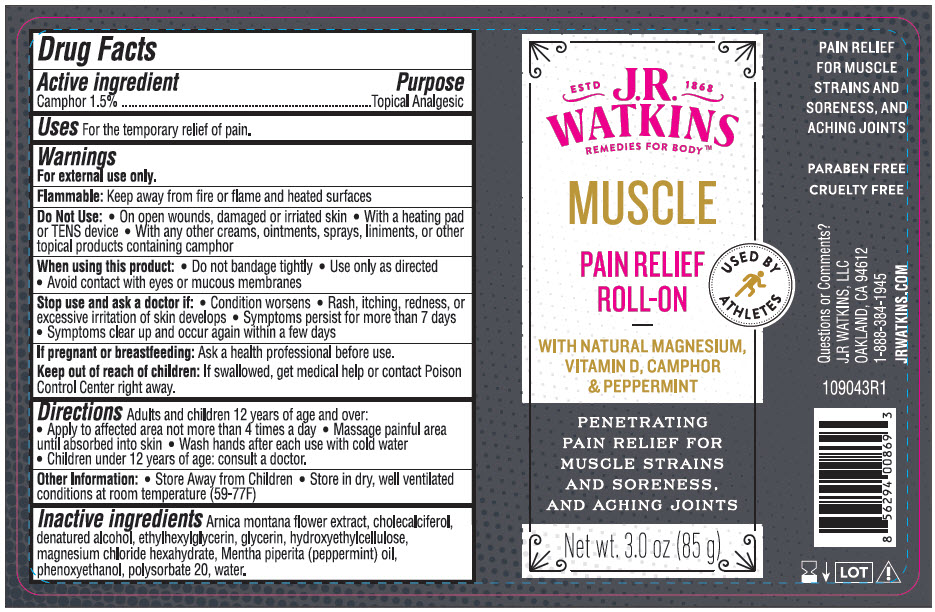 DRUG LABEL: Pain Relief Roll-On
NDC: 72342-190 | Form: GEL
Manufacturer: J.R. Watkins, LLC.
Category: otc | Type: HUMAN OTC DRUG LABEL
Date: 20240320

ACTIVE INGREDIENTS: CAMPHOR (NATURAL) 1.5 g/100 g
INACTIVE INGREDIENTS: ARNICA MONTANA FLOWER; CHOLECALCIFEROL; ALCOHOL; ETHYLHEXYLGLYCERIN; GLYCERIN; HYDROXYETHYL CELLULOSE, UNSPECIFIED; MAGNESIUM CHLORIDE; PEPPERMINT OIL; PHENOXYETHANOL; POLYSORBATE 20; WATER

Pain Relief Roll-On
Muscle

Drug Facts

Active Ingredient

Camphor 1.5%

Purpose

Topical Analgesic

Uses

For the temporary relief of pain

Warnings

For external use only.

Flammable:Keep away from fire or flame and heated surfaces.

Do not use

- On open wounds, damaged or irritated skin
- With a heading pad or TENS device
- With any other creams, ointments, sprays, liniments, or other topical products containing camphor

When using this product

- Do not bandage tightly
- Use only as directed
- Avoid contact with eyes or mucous membranes

Stop use and ask a doctor if

- Condition worsens
- Rash, itching, redness, or excessive irritation of skin develops
- Symptoms persist for more than 7 days
- Symptoms clear up and occur again within a few days

If pregnant or breastfeeding

Ask a health professional before use.

Keep out of reach of children. If swallowed, get medical help or contact a Poison Control Center right away.

Directions

- Adults and children 12 years of age and older:
- Apply to affected area not more 4 times a day
- Massage painful area until absorbed into skin
- Wash hands after each use with cold water
- Children under 12 years of age: consult a doctor.

Other information

- Store away from children
- Store in dry, well-ventilated conditions at room temperature (59-77°F)

Inactive ingredients

Arnica montana flower extract, cholecalciferol, denatured alcohol, ethylhexylglycerin, glycerin, hydroxyethylcellulose, magnesium chloride hexahydrate, Mentha piperita (peppermint) oil, phenoxyethanol, polysorbate 20, water

Questions or Comments?

J.R. WATKINS, LLC
OAKLAND, CA 94612
1-888-384-1945
JRWATKINS.COM

PRINCIPAL DISPLAY PANEL - 85 g Bottle Label

ESTD 1868
J.R.
WATKINS
REMEDIES FOR BODY™

MUSCLE

PAIN RELIEF
ROLL-ON

USED BY
ATHLETES

WITH NATURAL MAGNESIUM,
VITAMIN D, CAMPHOR
& PEPPERMINT

PENETRATING
PAIN RELIEF FOR
MUSCLE STRAINS
AND SORENESS,
AND ACHING JOINTS

Net wt. 3.0 oz (85 g)